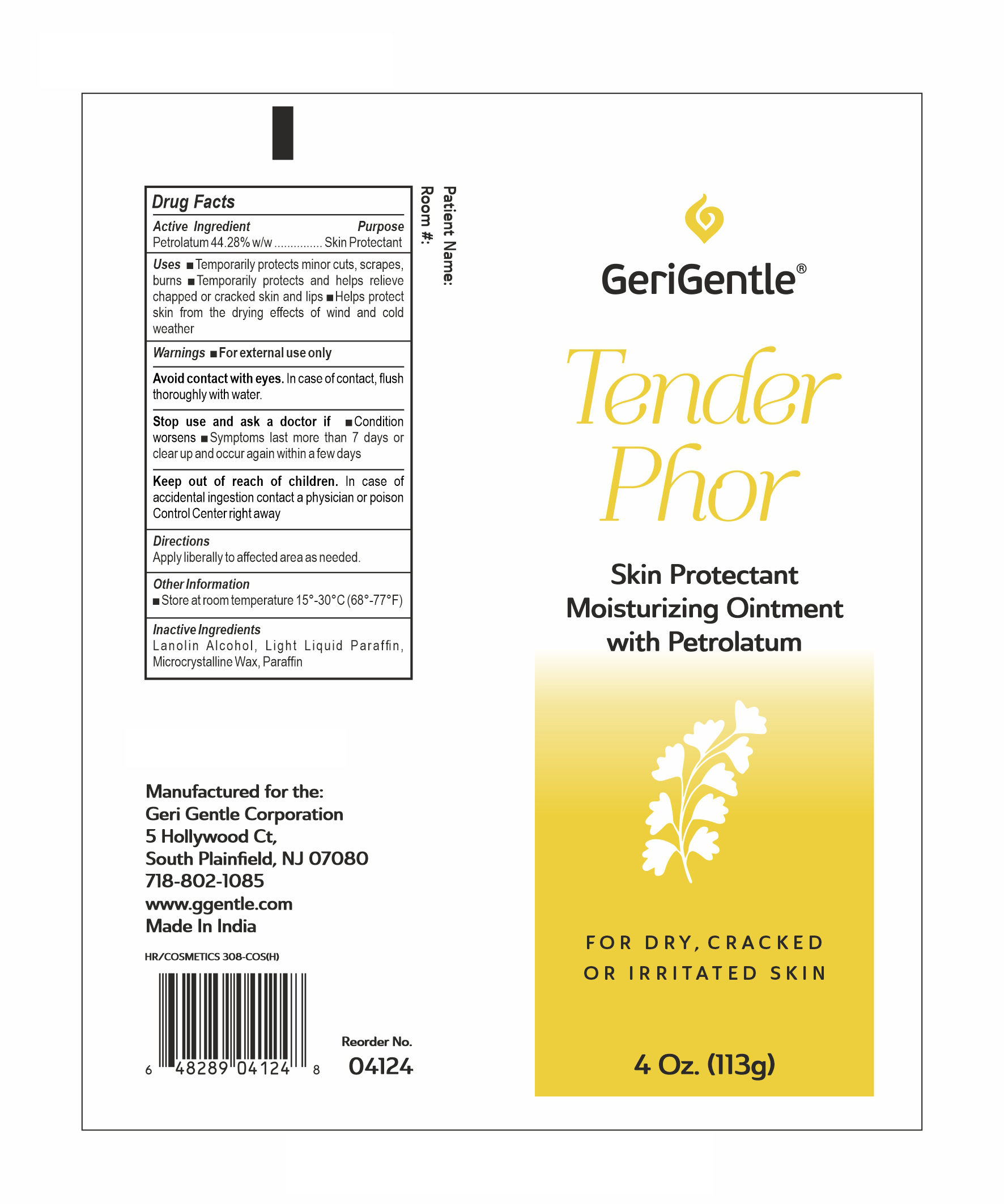 DRUG LABEL: Tenderphor
NDC: 69771-014 | Form: OINTMENT
Manufacturer: GERI-GENTLE CORPORATION
Category: otc | Type: HUMAN OTC DRUG LABEL
Date: 20251023

ACTIVE INGREDIENTS: PETROLATUM 44.28 g/100 g
INACTIVE INGREDIENTS: MICROCRYSTALLINE WAX; LIGHT MINERAL OIL; LANOLIN ALCOHOLS; PARAFFIN

TENDERPHOR

Active Ingredient:

Petrolatum 44.28%

Purpose:

Skin Protectant

Uses:

- Temporarily protects minor cuts, scrapes, burns.
- Temporarily protects and helps relieve chapped or cracked skin and lips.
- Helps protect skin from the drying effects of wind and cold weather.

Warnings:

For external use only.

Warnings:

Avoid contact with eyes.In case of contact, flush thoroughly with water.

Warnings:

Stop and ask a doctor if

- condition worsens
- symptoms last more than 7 days or clear up and occur again within a few days

Warnings:

Do not useon deep or puncture wounds, animal bites, or serious wounds.

Warnings:

Keep out of reach of children.

Incase of accidental ingestion contact a Physician or Poison Control Center right away.

Directions:

Apply liberally to affected area as needed.

Other Information:

■Store at room temperature 15°-30°C (68°-77°F)

Inactive Ingredients:

Lanolin Alcohol, Light Liquid Parafﬁn, Microcrystalline Wax, Parafﬁn